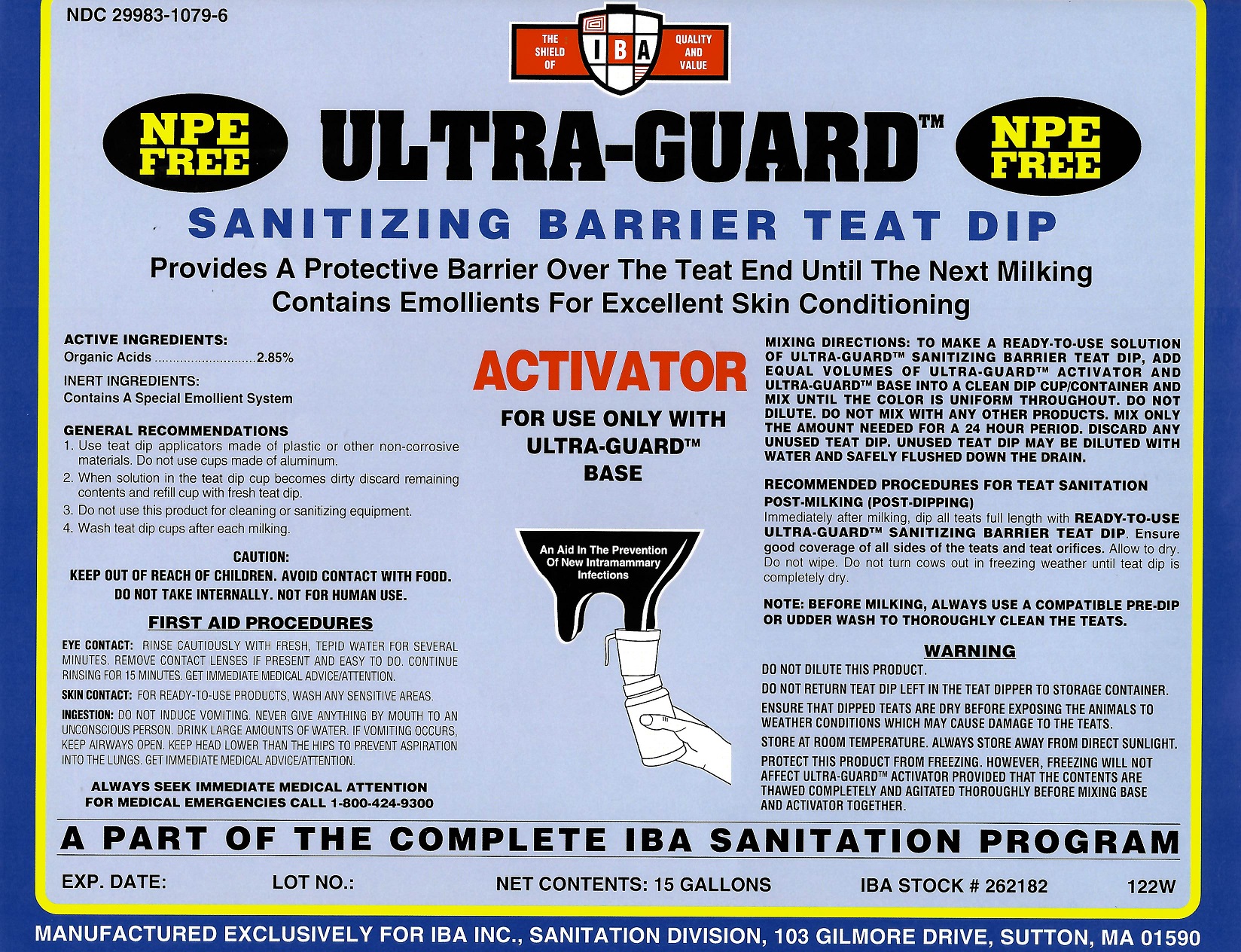 DRUG LABEL: Ultra-Guard Activator
NDC: 29983-1079 | Form: LIQUID
Manufacturer: IBA
Category: animal | Type: OTC ANIMAL DRUG LABEL
Date: 20251211

ACTIVE INGREDIENTS: LACTIC ACID 2.85 kg/100 kg

Ultra-Guard Activator

Active Ingredient

Organic Acids 2.85%

Inert Ingredients

Contains a special emollient system

Mixing Directions

To make a ready-to-use solution of Ultra-Guard Sanitizing Barrier Teat dip, add equal volumes of Ultra-Guard Activator and Ultra-Guard Base into a clean dip cup/container and mix until the color is uniform throughout. Do not dilute. Mix only the amount needed for one milking of the herd. Discard any unused teat dip. Do not mix with any other products.

Recommended procedures for teat sanitation

POST-MILKING (POST-DIPPING)
Immediately after milking, dip all teats full length with READY-TO-USE ULTRA-GUARD SANITIZING BARRIER TEAT DIP. Ensure good coverage of all sides of the teats and teat orifices. Allow to dry. Do not wipe. Do not turn cows out in freezing weather until teat dip is completely dry.

NOTE: Before milking, use a compatible teat dip or udder wash to thoroughly clean the teats.

First Aid

EYE CONTACT: Rinse cautiously with fresh, tepid water for several minutes. Remove contact lenses if present and easy to do. Continue rinsing for 15 minutes. Get immediate medical advice/attention. SKIN CONTACT: For RTU products wash any sensitive areas. INGESTION: Do not induce vomiting. Never give anything by mouth to an unconscious person. Drink large amounts of water. If vomiting occurs, keep airways open. Keep head lower than the hips to prevent aspiration into the lungs. Get immediate medical advice/attention.

Caution

Keep out of reach of children. Avoid contact with food. Do not take internally.

Warning

Do not dilute this product.
Do not return teat dip left in the teat dipper to storage container.
Ensure that dipped teats are dry before exposing the animals to weather conditions which may cause damage to the teats.
Protect this product from freezing. Store at room temperature. Always store away from direct sunlight.